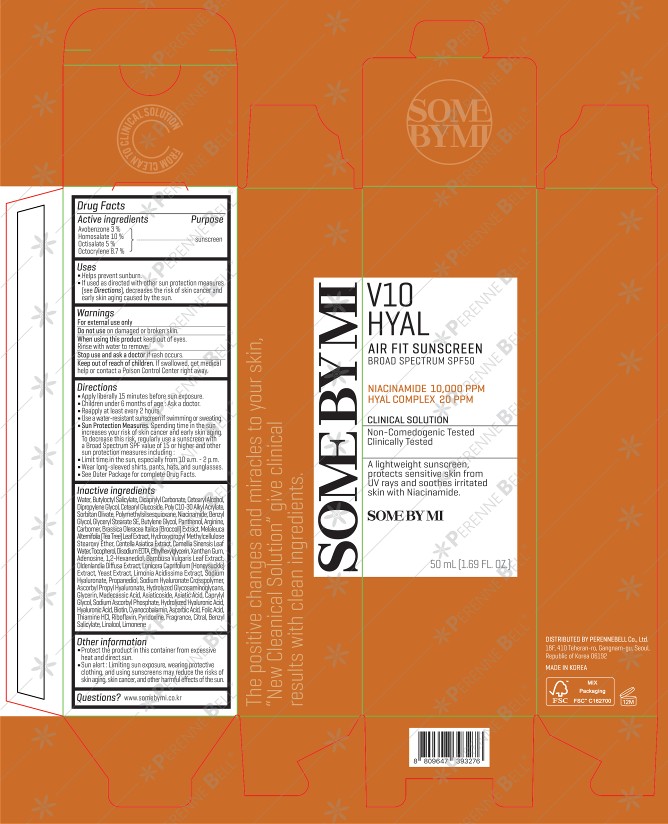 DRUG LABEL: SOME BY MI V10 HYAL AIR FIT SUNSCREEN
NDC: 74472-235 | Form: CREAM
Manufacturer: PERENNEBELL
Category: otc | Type: HUMAN OTC DRUG LABEL
Date: 20251113

ACTIVE INGREDIENTS: AVOBENZONE 3 g/50 mL; HOMOSALATE 10 g/50 mL; OCTISALATE 5 g/50 mL; OCTOCRYLENE 8.7 g/50 mL
INACTIVE INGREDIENTS: WATER 27.585 mL/50 mL

Directions
■ Apply liberally 15 minutes before sun exposure.

■ Children under 6 months of age: Ask a doctor.

■ Reapply at least every 2 hours.
■ Use a water-resistant sunscreen if swimming or sweating.

■ Sun Protection Measures. Spending time in the sun increases your risk of skin cancer and early skin aging. To decrease this risk, regularly use a sunscreen with a Broad Spectrum SPF value of 15 or higher and other sun protection measures including:
■ Limit time in the sun, especially from 10 a.m. - 2 p.m.

■ Wear long-sleeved shirts, pants, hats, and sunglasses.

■ See Outer Package for complete Drug Facts.

Uses
■ Helps prevent sunburn.
■ If used as directed with other sun protection measures [see Directions], decreases the risk of skin cancer and early skin aging caused by the sun.

INACTIVE INGREDIENT

Water, Butyloctyl Salicylate, Dicaprylyl Carbonate, Cetearyl Alcohol, Dipropylene Glycol, Cetearyl Glucoside, Poly C10-30 Alkyl Acrylate, Sorbitan Olivate, Polymethylsilsesquioxane, Niacinamide, Benzyl Glycol, Glyceryl Stearate SE, Butylene Glycol, Panthenol, Arginine, Carbomer, Brassica Oleracea Italica (Broccoli) Extract, Melaleuca Alternifolia [Tea Tree) Leaf Extract, Hydroxypropyl Methylcellulose Stearoxy Ether, Centella Asiatica Extract, Camellia Sinensis Leaf Water, Tocopherol, Disodium EDTA, Ethylhexylglycerin, Xanthan Gum, Adenosine, 1,2-Hexanediol, Bambusa Vulgaris Leaf Extract, Oldenlandia Diffusa Extract, Lonicera Caprifolium (Honeysuckle] Extract, Yeast Extract, Limonia Acidissima Extract, Sodium Hyaluronate, Propanediol, Sodium Hyaluronate Crosspolymer, Ascorbyl Propyl Hyaluronate, Hydrolyzed Glycosaminoglycans, Glycerin, Madecassic Acid, Asiaticoside, Asiatic Acid, Caprylyl Glycol, Sodium Ascorbyl Phosphate, Hydrolyzed Hyaluronic Acid, Hyaluronic Acid, Biotin, Cyanocobalamin, Ascorbic Acid, Folic Acid, Thiamine HCI, Riboflavín, Pyridoxine, Fragrance, Citral, Benzyl Salicylate, Linalool, Limonene

ACTIVE INGREDIENT

Avobenzone 3%

Homosalate 10%

Octisalate 5%

Octocrylene 8.7%

PURPOSE

Sunscreen

Keep out of reach of children. If swallowed, get medical help or contact a Poison Control Center right away.

WARNINGS

For external use only

Uses
■ Helps prevent sunburn.
■ If used as directed with other sun protection measures [see Directions], decreases the risk of skin cancer and early skin aging caused by the sun.

OTHER SAFETY INFORMATION

■ Protect the product in this container from excessive heat and direct sun.

■ Sun alert: Limitng sun exposure, wearing protective clothing, and using sunscreens may reduce the risks of skin aging, skin cancer, and other harmful effects of the sun.

Do not use on damaged or broken skin.

Stop use and ask a doctor if rash occurs.

When using this product keep out of eyes. Rinse with water to remove.